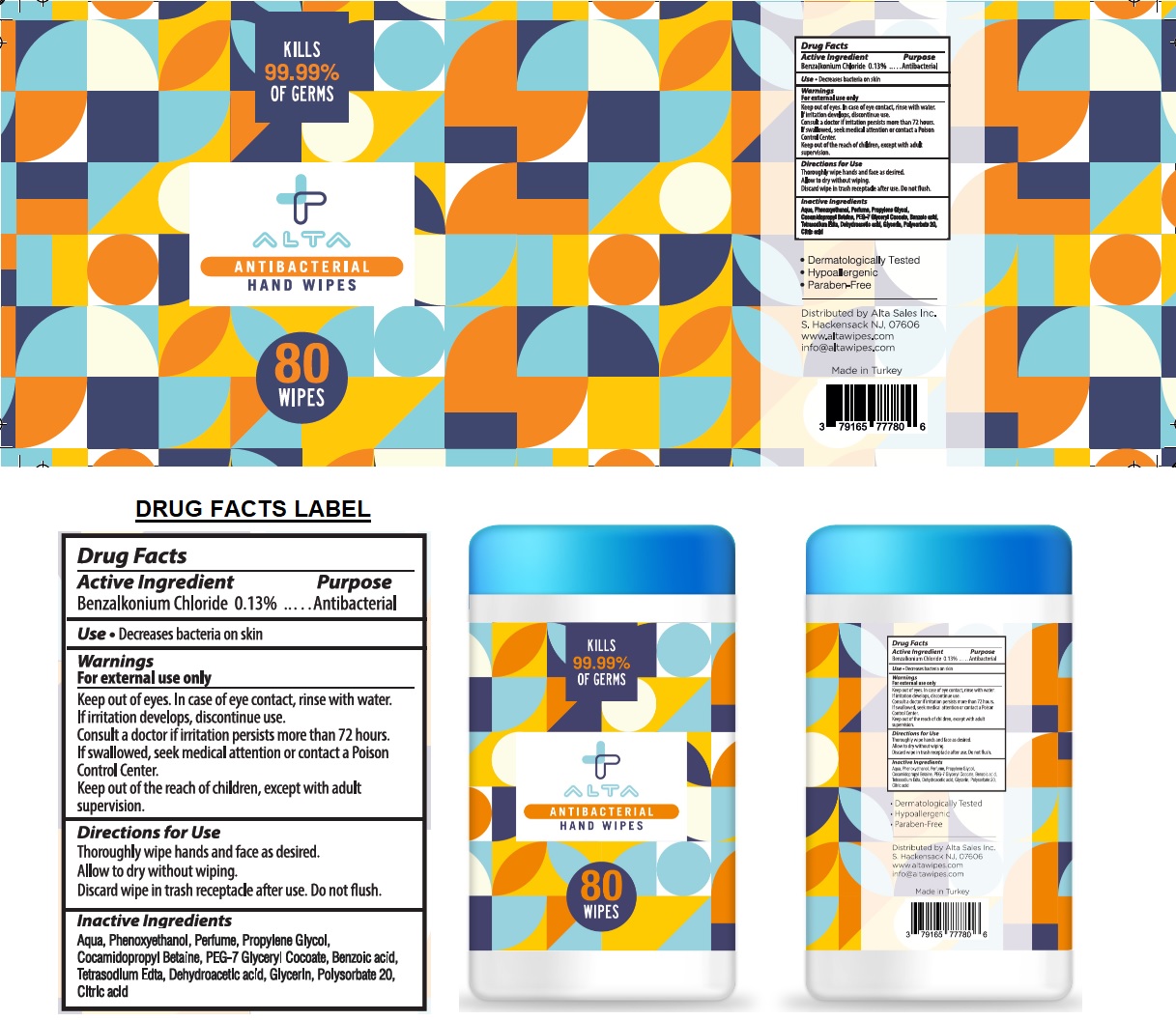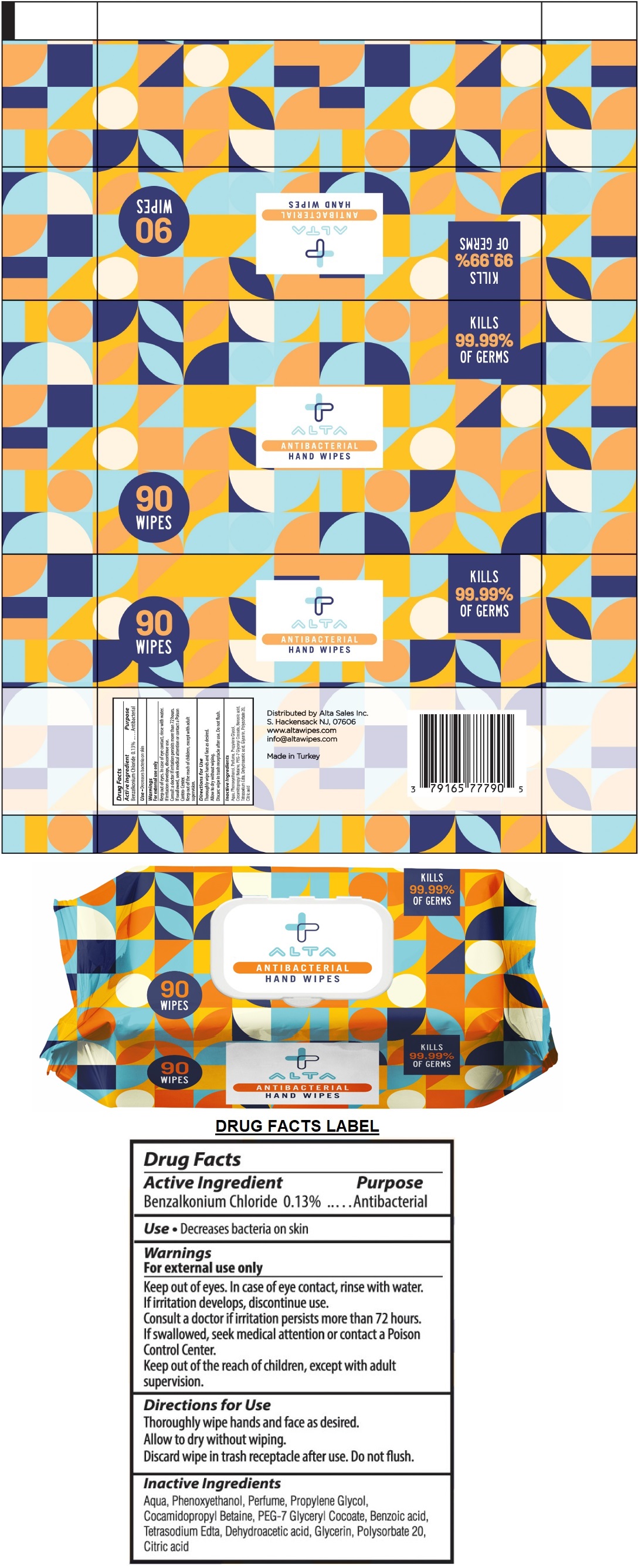 DRUG LABEL: ALTA ANTIBACTERIAL HAND WIPES
NDC: 79165-777 | Form: CLOTH
Manufacturer: Alta Sales Inc
Category: otc | Type: HUMAN OTC DRUG LABEL
Date: 20230619

ACTIVE INGREDIENTS: BENZALKONIUM CHLORIDE 0.13 g/100 g
INACTIVE INGREDIENTS: WATER; PHENOXYETHANOL; PROPYLENE GLYCOL; COCAMIDOPROPYL BETAINE; PEG-7 GLYCERYL COCOATE; BENZOIC ACID; EDETATE SODIUM; DEHYDROACETIC ACID; GLYCERIN; POLYSORBATE 20; CITRIC ACID MONOHYDRATE

ALTA ANTIBACTERIAL HAND WIPES

Active Ingredient

Benzalkonium Chloride 0.13%

Purpose

Antibacterial

Use

- Decreases bacteria on skin

Warnings

For external use only

Keep out of eyes. In case of eye contact, rinse with water.

If irritation develops, discontinue use.

Consult a doctor if irritation persists more than 72 hours.

If swallowed, seek medical attention or contact a Poison Control Center.

KEEP OUT OF REACH OF CHILDREN

Keep out of the children, except with adult supervision.

Directions for use

Thoroughly wipe hands and face as desired.

Allow to dry without wiping.

Discard wipe in trash receptacle after use. Do not flush.

Inactive ingredients

Aqua, Phenoxyethanol, Perfume, Propylene Glycol, Cocamidopropyl Betaine, PEG-7 Glyceryl Cocoate, Benzoic acid, Tetrasodium Edta, Dehydroacetic acid, Glycerin, Polysorbate 20, Citric acid

KILLS 99.99% OF GERMS

Distributed by Alta Sales Inc.

S. Hackensack NJ, 07606

www.altawipes.com

info@altawipes.com

Made in Turkey